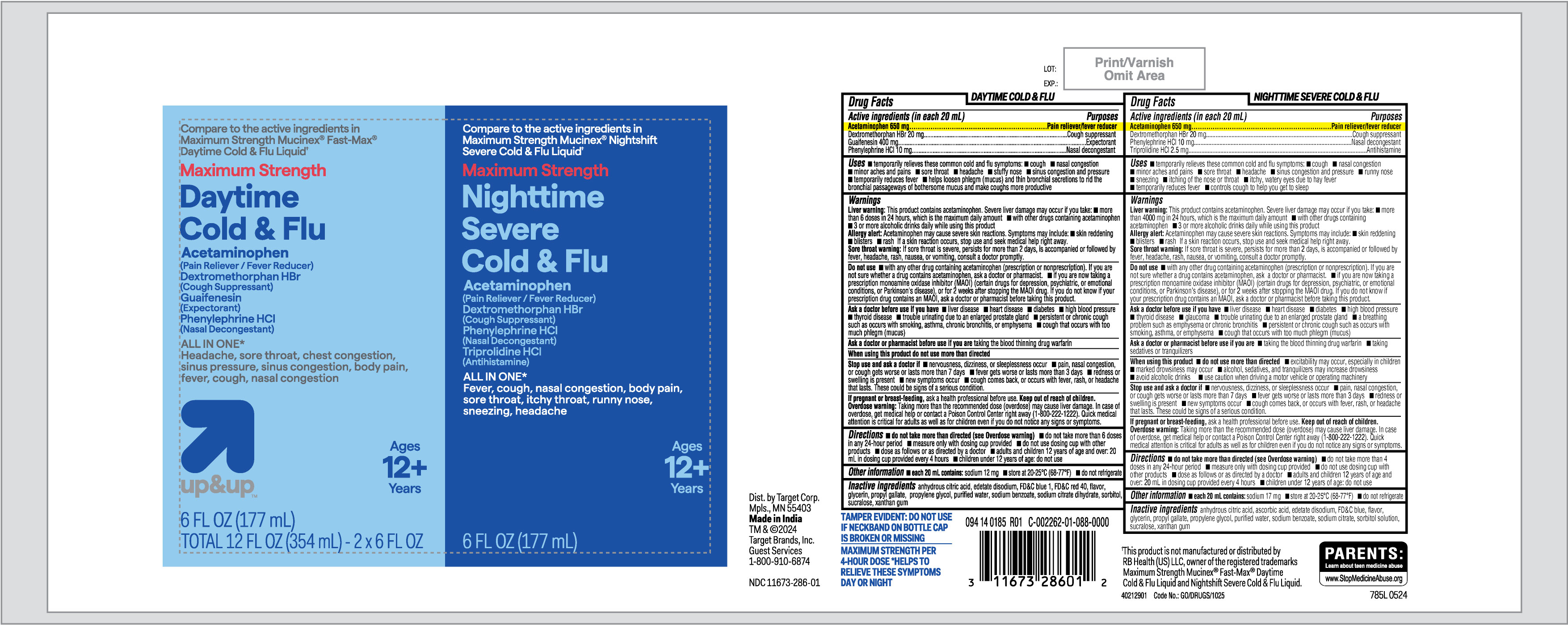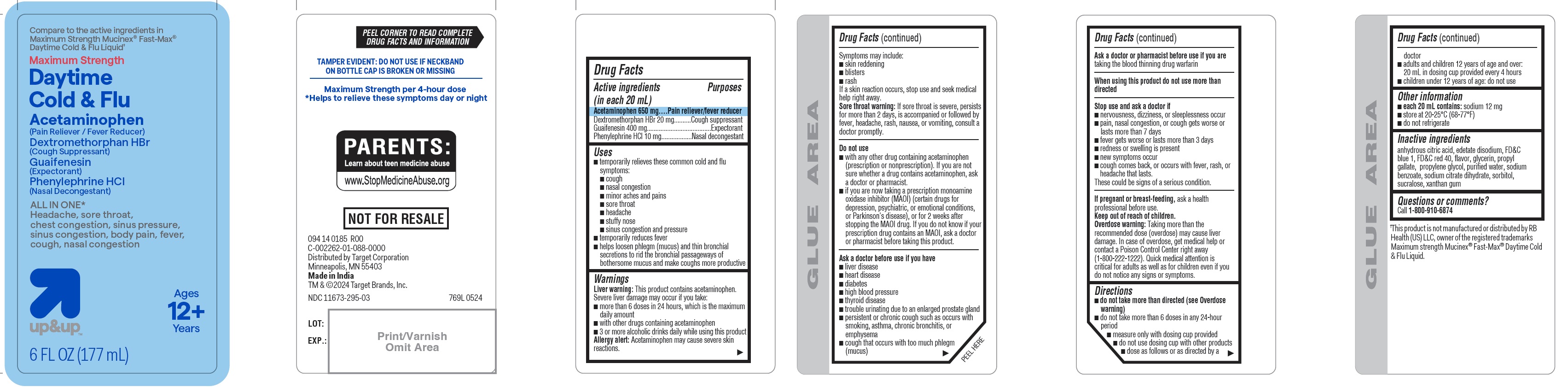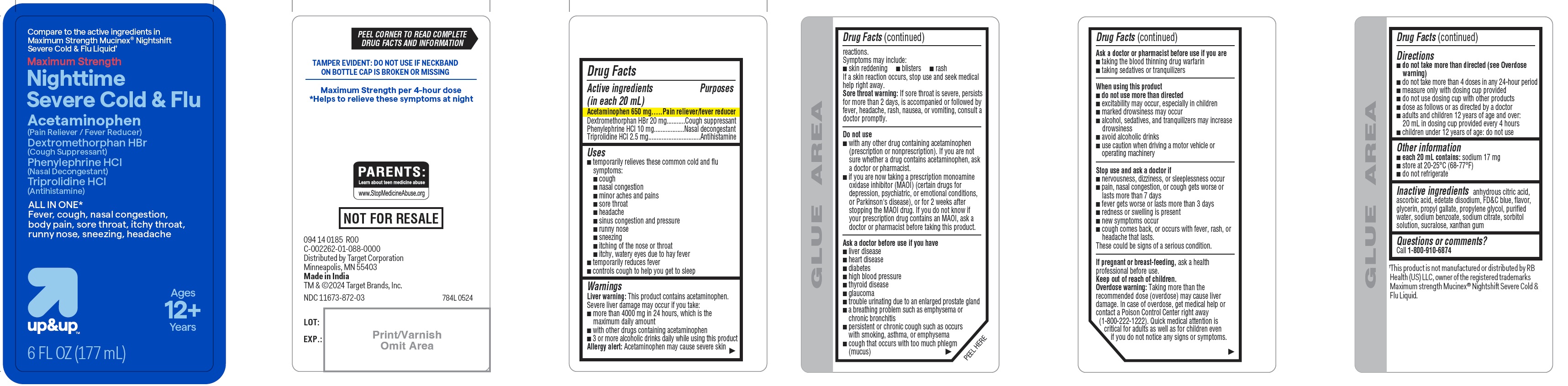 DRUG LABEL: Maximum Strength Daytime Cold and Flu and Nighttime Severe Cold and Flu
NDC: 11673-286 | Form: KIT | Route: ORAL
Manufacturer: TARGET CORPORATION
Category: otc | Type: HUMAN OTC DRUG LABEL
Date: 20240822

ACTIVE INGREDIENTS: ACETAMINOPHEN 650 mg/20 mL; DEXTROMETHORPHAN HYDROBROMIDE 20 mg/20 mL; PHENYLEPHRINE HYDROCHLORIDE 10 mg/20 mL; TRIPROLIDINE HYDROCHLORIDE 2.5 mg/20 mL; ACETAMINOPHEN 650 mg/20 mL; DEXTROMETHORPHAN HYDROBROMIDE 20 mg/20 mL; GUAIFENESIN 400 mg/20 mL; PHENYLEPHRINE HYDROCHLORIDE 10 mg/20 mL
INACTIVE INGREDIENTS: GLYCERIN; SODIUM CITRATE; ANHYDROUS CITRIC ACID; ASCORBIC ACID; EDETATE DISODIUM; FD&C BLUE NO. 1; PROPYLENE GLYCOL; SODIUM BENZOATE; SORBITOL; SUCRALOSE; WATER; XANTHAN GUM; PROPYL GALLATE; ANHYDROUS CITRIC ACID; EDETATE DISODIUM; FD&C BLUE NO. 1; FD&C RED NO. 40; GLYCERIN; PROPYL GALLATE; PROPYLENE GLYCOL; WATER; SODIUM BENZOATE; SORBITOL; SUCRALOSE; TRISODIUM CITRATE DIHYDRATE; XANTHAN GUM

Target Daytime Cold & Flu and Nighttime Severe Cold & Flu Liquid

Drug Facts

Daytime Cold & Flu

ACTIVE INGREDIENT

Daytime Cold & Flu

Active ingredients (in each 20 mL)

Acetaminophen 650 mg

Dextromethorphan HBr 20 mg

Guaifenesin 400 mg

Phenylephrine HCl 10 mg

Nighttime Severe Cold and Flu

Active ingredients (in each 20 mL)

Acetaminophen 650 mg

Dextromethorphan HBr 20 mg

Phenylephrine HCl 10 mg

Triprolidine HCl 2.5 mg

Purposes

Daytime Cold & Flu

Pain reliever/fever reducer

Cough suppressant

Expectorant

Nasal decongestant

Nighttime Severe Cold & Flu

Pain reliever/fever reducer

Cough suppressant

Nasal decongestant

Antihistamine

Uses

Daytime Cold & Flu

temporarily relieves these common cold and flu symptoms:

- cough
- nasal congestion
- minor aches and pains
- sore throat
- headache
- stuffy nose
- sinus congestion and pressure

temporarily reduces fever
helps loosen phlegm (mucus) and thin bronchial secretions to rid the bronchial passageways of bothersome mucus and make coughs more productive

Nighttime Severe Cold & Flu

temporarily relieves these common cold and flu symptoms:

- cough
- nasal congestion
- minor aches and pains
- sore throat
- headache
- sinus congestion and pressure
- runny nose
- sneezing
- itching of the nose or throat
- itchy, watery eyes due to hay fever

temporarily reduces fever
controls cough to help you get to sleep

Warnings

Liver warning

Daytime Cold & Flu

Liver warning: This product contains acetaminophen. Severe liver damage may occur if you take:

- more than 6 doses in 24 hours, which is the maximum daily amount
- with other drugs containing acetaminophen
- 3 or more alcoholic drinks daily while using this product

Nighttime Severe Cold & Flu

Liver warning: This product contains acetaminophen. Severe liver damage may occur if you take:

- more than 4000 mg in 24 hours, which is the maximum daily amount
- with other drugs containing acetaminophen
- 3 or more alcoholic drinks daily while using this product

Allergy alert

Acetaminophen may cause severe skin reactions.

Symptoms may include:

- skin reddening
- blisters
- rash

If a skin reaction occurs, stop use and seek medical help right away.

Sore throat warning

If sore throat is severe, persists for more than 2 days, is accompanied or followed by fever, headache, rash, nausea, or vomiting, consult a doctor promptly.

Do not use

- with any other drug containing acetaminophen (prescription or nonprescription). If you are not sure whether a drug contains acetaminophen, ask a doctor or pharmacist.
- if you are now taking a prescription monoamine oxidase inhibitor (MAOI) (certain drugs for depression, psychiatric, or emotional conditions, or Parkinson's disease), or for 2 weeks after stopping the MAOI drug. If you do not know if your prescription drug contains an MAOI, ask a doctor or pharmacist before taking this product.

Ask a doctor before use if you have

Daytime Cold & Flu

- liver disease
- heart disease
- diabetes
- high blood pressure
- thyroid disease
- trouble urinating due to an enlarged prostate gland
- persistent or chronic cough such as occurs with smoking, asthma, chronic bronchitis, or emphysema
- cough that occurs with too much phlegm (mucus)

Nighttime Severe Cold & Flu

- liver disease
- heart disease
- diabetes
- high blood pressure
- thyroid disease
- glaucoma
- trouble urinating due to an enlarged prostate gland
- a breathing problem such as emphysema or chronic bronchitis
- persistent or chronic cough such as occurs with smoking, asthma, or emphysema
- cough that occurs with too much phlegm (mucus)

Ask a doctor or pharmacist before use if you are

Daytime Cold & Flu

- taking the blood thinning drug warfarin

Nighttime Severe Cold and Flu

- taking the blood thinning drug warfarin
- taking sedatives or tranquilizers

When using this product

- do not use more than directed
- excitability may occur, especially in children (Nightshift Severe Cold & Flu only)
- marked drowsiness may occur (Nightshift Severe Cold & Flu only)
- alcohol, sedatives, and tranquilizers may increase drowsiness (Nightshift Severe Cold & Flu only)
- avoid alcoholic drinks (Nightshift Severe Cold & Flu only)
- use caution when driving a motor vehicle or operating machinery (Nightshift Severe Cold & Flu only)

Stop use and ask a doctor if

- nervousness, dizziness, or sleeplessness occur
- pain, nasal congestion, or cough gets worse or lasts more than 7 days
- fever gets worse or lasts more than 3 days
- redness or swelling is present
- new symptoms occur
- cough comes back, or occurs with fever, rash, or headache that lasts.

These could be signs of a serious condition.

PREGNANCY OR BREAST FEEDING

If pregnant or breast-feeding,ask a health professional before use.

Keep out of reach of children.

Overdose warning

Overdose warning: Taking more than the recommended dose (overdose) may cause liver damage. In case of overdose, get medical help or contact a Poison Control Center right away (1-800-222-1222). Quick medical attention is critical for adults as well as for children even if you do not notice any signs or symptoms.

Directions

Daytime Cold & Flu

- do not take more than directed (see Overdose warning)
- do not take more than 6 doses in any 24-hour period
- measure only with dosing cup provided
- do not use dosing cup with other products
- dose as follows or as directed by a doctor
- adults and children 12 years of age and over: 20 mL in dosing cup provided every 4 hours
- children under 12 years of age: do not use

Nighttime Severe Cold and Flu

- do not take more than directed (see Overdose warning)
- do not take more than 4 doses in any 24-hour period
- measure only with dosing cup provided
- do not use dosing cup with other products
- dose as follows or as directed by a doctor
- adults and children 12 years of age and over: 20 mL in dosing cup provided every 4 hours
- children under 12 years of age: do not use

Other information

Daytime Cold & Flu

- each 20 mL contains: sodium 12 mg
- store at 20-25°C (68-77°F)
- do not refrigerate

Nighttime Severe Cold and Flu

- each 20 mL contains: sodium 17 mg
- store at 20-25°C (68-77°F)
- do not refrigerate

Inactive ingredients

Daytime Cold & Flu

anhydrous citric acid, edetate disodium, FD&C blue 1, FD&C red 40, flavor, glycerin, propyl gallate, propylene glycol, purified water, sodium benzoate, sodium citrate dihydrate, sorbitol, sucralose, xanthan gum

Nighttime Severe Cold and Flu

anhydrous citric acid, ascorbic acid, edetate disodium, FD&C blue, flavor, glycerin, propyl gallate, propylene glycol, purified water, sodium benzoate, sodium citrate, sorbitol solution, sucralose, xanthan gum

Questions or comments?

Call 1-800-910-6874